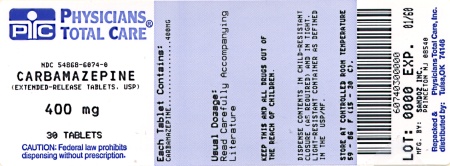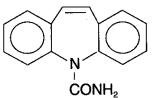 DRUG LABEL: Carbamazepine
NDC: 54868-6074 | Form: TABLET, EXTENDED RELEASE
Manufacturer: Physicians Total Care, Inc.
Category: prescription | Type: HUMAN PRESCRIPTION DRUG LABEL
Date: 20100510

ACTIVE INGREDIENTS: CARBAMAZEPINE 400 mg/1 1
INACTIVE INGREDIENTS: DEXTRATES; MAGNESIUM STEARATE; MANNITOL; POLYETHYLENE GLYCOL; SODIUM LAURYL SULFATE

Carbamazepine USP

Extended-Release Tablets 100 mg, 200 mg, 400 mg

Rx only

Prescribing Information

WARNINGS

SERIOUS DERMATOLOGIC REACTIONS AND HLA-B*1502 ALLELE

SERIOUS AND SOMETIMES FATAL DERMATOLOGIC REACTIONS, INCLUDING TOXIC EPIDERMAL NECROLYSIS (TEN) AND STEVENS-JOHNSON SYNDROME (SJS), HAVE BEEN REPORTED DURING TREATMENT WITH CARBAMAZEPINE. THESE REACTIONS ARE ESTIMATED TO OCCUR IN 1 TO 6 PER 10,000 NEW USERS IN COUNTRIES WITH MAINLY CAUCASIAN POPULATIONS, BUT THE RISK IN SOME ASIAN COUNTRIES IS ESTIMATED TO BE ABOUT 10 TIMES HIGHER. STUDIES IN PATIENTS OF CHINESE ANCESTRY HAVE FOUND A STRONG ASSOCIATION BETWEEN THE RISK OF DEVELOPING SJS/TEN AND THE PRESENCE OF HLA-B*1502, AN INHERITED ALLELIC VARIANT OF THE HLA-B GENE. HLA-B*1502 IS FOUND ALMOST EXCLUSIVELY IN PATIENTS WITH ANCESTRY ACROSS BROAD AREAS OF ASIA. PATIENTS WITH ANCESTRY IN GENETICALLY AT-RISK POPULATIONS SHOULD BE SCREENED FOR THE PRESENCE OF HLA-B*1502 PRIOR TO INITIATING TREATMENT WITH CARBAMAZEPINE. PATIENTS TESTING POSITIVE FOR THE ALLELE SHOULD NOT BE TREATED WITH CARBAMAZEPINE UNLESS THE BENEFIT CLEARLY OUTWEIGHS THE RISK (SEE WARNINGS AND PRECAUTIONS, LABORATORY TESTS).

APLASTIC ANEMIA AND AGRANULOCYTOSIS

APLASTIC ANEMIA AND AGRANULOCYTOSIS HAVE BEEN REPORTED IN ASSOCIATION WITH THE USE OF CARBAMAZEPINE. DATA FROM A POPULATION-BASED CASE CONTROL STUDY DEMONSTRATE THAT THE RISK OF DEVELOPING THESE REACTIONS IS 5-8 TIMES GREATER THAN IN THE GENERAL POPULATION. HOWEVER, THE OVERALL RISK OF THESE REACTIONS IN THE UNTREATED GENERAL POPULATION IS LOW, APPROXIMATELY SIX PATIENTS PER ONE MILLION POPULATION PER YEAR FOR AGRANULOCYTOSIS AND TWO PATIENTS PER ONE MILLION POPULATION PER YEAR FOR APLASTIC ANEMIA.

ALTHOUGH REPORTS OF TRANSIENT OR PERSISTENT DECREASED PLATELET OR WHITE BLOOD CELL COUNTS ARE NOT UNCOMMON IN ASSOCIATION WITH THE USE OF CARBAMAZEPINE, DATA ARE NOT AVAILABLE TO ESTIMATE ACCURATELY THEIR INCIDENCE OR OUTCOME. HOWEVER, THE VAST MAJORITY OF THE CASES OF LEUKOPENIA HAVE NOT PROGRESSED TO THE MORE SERIOUS CONDITIONS OF APLASTIC ANEMIA OR AGRANULOCYTOSIS.

BECAUSE OF THE VERY LOW INCIDENCE OF AGRANULOCYTOSIS AND APLASTIC ANEMIA, THE VAST MAJORITY OF MINOR HEMATOLOGIC CHANGES OBSERVED IN MONITORING OF PATIENTS ON CARBAMAZEPINE ARE UNLIKELY TO SIGNAL THE OCCURRENCE OF EITHER ABNORMALITY. NONETHELESS, COMPLETE PRETREATMENT HEMATOLOGICAL TESTING SHOULD BE OBTAINED AS A BASELINE. IF A PATIENT IN THE COURSE OF TREATMENT EXHIBITS LOW OR DECREASED WHITE BLOOD CELL OR PLATELET COUNTS, THE PATIENT SHOULD BE MONITORED CLOSELY. DISCONTINUATION OF THE DRUG SHOULD BE CONSIDERED IF ANY EVIDENCE OF SIGNIFICANT BONE MARROW DEPRESSION DEVELOPS.

Before prescribing carbamazepine, the physician should be thoroughly familiar with the details of this prescribing information, particularly regarding use with other drugs, especially those which accentuate toxicity potential.

DESCRIPTION

Carbamazepine USP, is an anticonvulsant and specific analgesic for trigeminal neuralgia, available for oral administration as chewable tablets of 100 mg, tablets of 200 mg, extended-release tablets of 100, 200, and 400 mg, and as a suspension of 100 mg/5 mL (teaspoon). Its chemical name is 5H-dibenz[b,f ]azepine-5-carboxamide, and its structural formula is

Carbamazepine USP is a white to off-white powder, practically insoluble in water and soluble in alcohol and in acetone. Its molecular weight is 236.27.

Inactive Ingredients Extended-release tablets: cellulose compounds, dextrates, iron oxides, magnesium stearate, mannitol, polyethylene glycol, sodium lauryl sulfate, titanium dioxide (200-mg tablets only).

CLINICAL PHARMACOLOGY

In controlled clinical trials, carbamazepine has been shown to be effective in the treatment of psychomotor and grand mal seizures, as well as trigeminal neuralgia.

Mechanism of Action

Carbamazepine has demonstrated anticonvulsant properties in rats and mice with electrically and chemically induced seizures. It appears to act by reducing polysynaptic responses and blocking the post-tetanic potentiation. Carbamazepine greatly reduces or abolishes pain induced by stimulation of the infraorbital nerve in cats and rats. It depresses thalamic potential and bulbar and polysynaptic reflexes, including the linguomandibular reflex in cats. Carbamazepine is chemically unrelated to other anticonvulsants or other drugs used to control the pain of trigeminal neuralgia. The mechanism of action remains unknown.

The principal metabolite of carbamazepine, carbamazepine-10,11-epoxide, has anticonvulsant activity as demonstrated in several in vivo animal models of seizures. Though clinical activity for the epoxide has been postulated, the significance of its activity with respect to the safety and efficacy of carbamazepine has not been established.

Pharmacokinetics

In clinical studies, carbamazepine suspension, conventional tablets, and extended-release tablets delivered equivalent amounts of drug to the systemic circulation. However, the suspension was absorbed somewhat faster, and the extended-release tablet slightly slower, than the conventional tablet. The bioavailability of the extended-release tablet was 89% compared to suspension. Following a b.i.d. dosage regimen, the suspension provides higher peak levels and lower trough levels than those obtained from the conventional tablet for the same dosage regimen. On the other hand, following a t.i.d. dosage regimen, carbamazepine suspension affords steady-state plasma levels comparable to carbamazepine tablets given b.i.d. when administered at the same total mg daily dose. Following a b.i.d. dosage regimen, carbamazepine extended-release tablets afford steady-state plasma levels comparable to conventional carbamazepine tablets given q.i.d., when administered at the same total mg daily dose. Carbamazepine in blood is 76% bound to plasma proteins. Plasma levels of carbamazepine are variable and may range from 0.5-25 µg/mL, with no apparent relationship to the daily intake of the drug. Usual adult therapeutic levels are between 4 and 12 µg/mL. In polytherapy, the concentration of carbamazepine and concomitant drugs may be increased or decreased during therapy, and drug effects may be altered (see PRECAUTIONS, Drug Interactions). Following chronic oral administration of suspension, plasma levels peak at approximately 1.5 hours compared to 4-5 hours after administration of conventional carbamazepine tablets, and 3-12 hours after administration of carbamazepine extended-release tablets. The CSF/serum ratio is 0.22, similar to the 24% unbound carbamazepine in serum. Because carbamazepine induces its own metabolism, the half-life is also variable. Autoinduction is completed after 3-5 weeks of a fixed dosing regimen. Initial half-life values range from 25-65 hours, decreasing to 12-17 hours on repeated doses. Carbamazepine is metabolized in the liver. Cytochrome P450 3A4 was identified as the major isoform responsible for the formation of carbamazepine-10,11-epoxide from carbamazepine. After oral administration of ^14C-carbamazepine, 72% of the administered radioactivity was found in the urine and 28% in the feces. This urinary radioactivity was composed largely of hydroxylated and conjugated metabolites, with only 3% of unchanged carbamazepine.

The pharmacokinetic parameters of carbamazepine disposition are similar in children and in adults. However, there is a poor correlation between plasma concentrations of carbamazepine and carbamazepine dose in children. Carbamazepine is more rapidly metabolized to carbamazepine-10,11-epoxide (a metabolite shown to be equipotent to carbamazepine as an anticonvulsant in animal screens) in the younger age groups than in adults. In children below the age of 15, there is an inverse relationship between CBZ-E/CBZ ratio and increasing age (in one report from 0.44 in children below the age of 1 year to 0.18 in children between 10-15 years of age).

The effects of race and gender on carbamazepine pharmacokinetics have not been systematically evaluated.

INDICATIONS AND USAGE

Epilepsy

Carbamazepine is indicated for use as an anticonvulsant drug. Evidence supporting efficacy of carbamazepine as an anticonvulsant was derived from active drug-controlled studies that enrolled patients with the following seizure types:

1. Partial seizures with complex symptomatology (psychomotor, temporal lobe). Patients with these seizures appear to show greater improvement than those with other types.
2. Generalized tonic-clonic seizures (grand mal).
3. Mixed seizure patterns which include the above, or other partial or generalized seizures. Absence seizures (petit mal) do not appear to be controlled by carbamazepine (see PRECAUTIONS, General).

Trigeminal Neuralgia

Carbamazepine is indicated in the treatment of the pain associated with true trigeminal neuralgia.

Beneficial results have also been reported in glossopharyngeal neuralgia.

This drug is not a simple analgesic and should not be used for the relief of trivial aches or pains.

CONTRAINDICATIONS

Carbamazepine should not be used in patients with a history of previous bone marrow depression, hypersensitivity to the drug, or known sensitivity to any of the tricyclic compounds, such as amitriptyline, desipramine, imipramine, protriptyline, nortriptyline, etc. Likewise, on theoretical grounds its use with monoamine oxidase inhibitors is not recommended. Before administration of carbamazepine, MAO inhibitors should be discontinued for a minimum of 14 days, or longer if the clinical situation permits.

Coadministration of carbamazepine and nefazodone may result in insufficient plasma concentrations of nefazodone and its active metabolite to achieve a therapeutic effect. Coadministration of carbamazepine with nefazodone is contraindicated.

WARNINGS

Serious Dermatologic Reactions

Serious and sometimes fatal dermatologic reactions, including toxic epidermal necrolysis (TEN) and Stevens-Johnson syndrome (SJS), have been reported with carbamazepine treatment. The risk of these events is estimated to be about 1 to 6 per 10,000 new users in countries with mainly Caucasian populations. However, the risk in some Asian countries is estimated to be about 10 times higher. Carbamazepine should be discontinued at the first sign of a rash, unless the rash is clearly not drug-related. If signs or symptoms suggest SJS/TEN, use of this drug should not be resumed and alternative therapy should be considered.

SJS/TEN and HLA-B*1502 Allele

Retrospective case-control studies have found that in patients of Chinese ancestry there is a strong association between the risk of developing SJS/TEN with carbamazepine treatment and the presence of an inherited variant of the HLA-B gene, HLA-B*1502. The occurrence of higher rates of these reactions in countries with higher frequencies of this allele suggests that the risk may be increased in allele-positive individuals of any ethnicity.

Across Asian populations, notable variation exists in the prevalence of HLA-B*1502. Greater than 15% of the population is reported positive in Hong Kong, Thailand, Malaysia, and parts of the Philippines, compared to about 10% in Taiwan and 4% in North China. South Asians, including Indians, appear to have intermediate prevalence of HLA-B*1502, averaging 2 to 4%, but higher in some groups. HLA-B*1502 is present in less than 1% of the population in Japan and Korea.

HLA-B*1502 is largely absent in individuals not of Asian origin (e.g., Caucasians, African-Americans, Hispanics, and Native Americans).

Prior to initiating carbamazepine therapy, testing for HLA-B*1502 should be performed in patients with ancestry in populations in which HLA-B*1502 may be present. In deciding which patients to screen, the rates provided above for the prevalence of HLA-B*1502 may offer a rough guide, keeping in mind the limitations of these figures due to wide variability in rates even within ethnic groups, the difficulty in ascertaining ethnic ancestry, and the likelihood of mixed ancestry. Carbamazepine should not be used in patients positive for HLA-B*1502 unless the benefits clearly outweigh the risks. Tested patients who are found to be negative for the allele are thought to have a low risk of SJS/TEN (see WARNINGS and PRECAUTIONS, Laboratory Tests).

Over 90% of carbamazepine treated patients who will experience SJS/TEN have this reaction within the first few months of treatment. This information may be taken into consideration in determining the need for screening of genetically at-risk patients currently on carbamazepine.

The HLA-B*1502 allele has not been found to predict risk of less severe adverse cutaneous reactions from carbamazepine, such as anticonvulsant hypersensitivity syndrome or nonserious rash (maculopapular eruption [MPE]).

Limited evidence suggests that HLA-B*1502 may be a risk factor for the development of SJS/TEN in patients of Chinese ancestry taking other antiepileptic drugs associated with SJS/TEN. Consideration should be given to avoiding use of other drugs associated with SJS/TEN in HLA-B*1502 positive patients, when alternative therapies are otherwise equally acceptable.

Application of HLA-B*1502 genotyping as a screening tool has important limitations and must never substitute for appropriate clinical vigilance and patient management. Many HLA-B*1502-positive Asian patients treated with carbamazepine will not develop SJS/TEN, and these reactions can still occur infrequently in HLA-B*1502-negative patients of any ethnicity. The role of other possible factors in the development of, and morbidity from, SJS/TEN, such as antiepileptic drug (AED) dose, compliance, concomitant medications, comorbidities, and the level of dermatologic monitoring have not been studied.

Aplastic Anemia and Agranulocytosis

Patients with a history of adverse hematologic reaction to any drug may be particularly at risk of bone marrow depression.

Suicidal Behavior and Ideation

Antiepileptic drugs (AEDs), including carbamazepine, increase the risk of suicidal thoughts or behavior in patients taking these drugs for any indication. Patients treated with any AED for any indication should be monitored for the emergence or worsening of depression, suicidal thoughts or behavior, and/or any unusual changes in mood or behavior.

Pooled analyses of 199 placebo-controlled clinical trials (mono- and adjunctive therapy) of 11 different AEDs showed that patients randomized to one of the AEDs had approximately twice the risk (adjusted Relative Risk 1.8, 95% CI:1.2, 2.7) of suicidal thinking or behavior compared to patients randomized to placebo. In these trials, which had a median treatment duration of 12 weeks, the estimated incidence rate of suicidal behavior or ideation among 27,863 AED-treated patients was 0.43%, compared to 0.24% among 16,029 placebo-treated patients, representing an increase of approximately one case of suicidal thinking or behavior for every 530 patients treated. There were four suicides in drug-treated patients in the trials and none in placebo-treated patients, but the number is too small to allow any conclusion about drug effect on suicide.

The increased risk of suicidal thoughts or behavior with AEDs was observed as early as one week after starting drug treatment with AEDs and persisted for the duration of treatment assessed. Because most trials included in the analysis did not extend beyond 24 weeks, the risk of suicidal thoughts or behavior beyond 24 weeks could not be assessed.

The risk of suicidal thoughts or behavior was generally consistent among drugs in the data analyzed. The finding of increased risk with AEDs of varying mechanisms of action and across a range of indications suggests that the risk applies to all AEDs used for any indication. The risk did not vary substantially by age (5-100 years) in the clinical trials analyzed. Table 1 shows absolute and relative risk by indication for all evaluated AEDs.

Table 1 Risk by Indication for Antiepileptic Drugs in the Pooled Analysis

Indication | Placebo Patients with Events Per 1,000 Patients | Drug Patients with Events Per 1,000 Patients | Relative Risk: Incidence of Events in Drug Patients/Incidence in Placebo Patients | Risk Difference: Additional Drug Patients with Events Per 1,000 Patients
Epilepsy | 1.0 | 3.4 | 3.5 | 2.4
Psychiatric | 5.7 | 8.5 | 1.5 | 2.9
Other | 1.0 | 1.8 | 1.9 | 0.9
Total | 2.4 | 4.3 | 1.8 | 1.9

The relative risk for suicidal thoughts or behavior was higher in clinical trials for epilepsy than in clinical trials for psychiatric or other conditions, but the absolute risk differences were similar for the epilepsy and psychiatric indications.

Anyone considering prescribing carbamazepine or any other AED must balance the risk of suicidal thoughts or behavior with the risk of untreated illness. Epilepsy and many other illnesses for which AEDs are prescribed are themselves associated with morbidity and mortality and an increased risk of suicidal thoughts and behavior. Should suicidal thoughts and behavior emerge during treatment, the prescriber needs to consider whether the emergence of these symptoms in any given patient may be related to the illness being treated.

Patients, their caregivers, and families should be informed that AEDs increase the risk of suicidal thoughts and behavior and should be advised of the need to be alert for the emergence or worsening of the signs and symptoms of depression, any unusual changes in mood or behavior, or the emergence of suicidal thoughts, behavior, or thoughts about self-harm. Behaviors of concern should be reported immediately to healthcare providers.

General

Carbamazepine has shown mild anticholinergic activity; therefore, patients with increased intraocular pressure should be closely observed during therapy.

Because of the relationship of the drug to other tricyclic compounds, the possibility of activation of a latent psychosis and, in elderly patients, of confusion or agitation should be borne in mind.

The use of carbamazepine should be avoided in patients with a history of hepatic porphyria (e.g., acute intermittent porphyria, variegate porphyria, porphyria cutanea tarda). Acute attacks have been reported in such patients receiving carbamazepine therapy. Carbamazepine administration has also been demonstrated to increase porphyrin precursors in rodents, a presumed mechanism for the induction of acute attacks of porphyria.

As with all antiepileptic drugs, carbamazepine should be withdrawn gradually to minimize the potential of increased seizure frequency.

Usage in Pregnancy

Carbamazepine can cause fetal harm when administered to a pregnant woman.

Epidemiological data suggest that there may be an association between the use of carbamazepine during pregnancy and congenital malformations, including spina bifida. There have also been reports that associate carbamazepine with developmental disorders and congenital anomalies (e.g., craniofacial defects, cardiovascular malformations, hypospadias and anomalies involving various body systems). Developmental delays based on neurobehavioral assessments have been reported. In treating or counseling women of childbearing potential, the prescribing physician will wish to weigh the benefits of therapy against the risks. If this drug is used during pregnancy, or if the patient becomes pregnant while taking this drug, the patient should be apprised of the potential hazard to the fetus.

Retrospective case reviews suggest that, compared with monotherapy, there may be a higher prevalence of teratogenic effects associated with the use of anticonvulsants in combination therapy. Therefore, if therapy is to be continued, monotherapy may be preferable for pregnant women.

In humans, transplacental passage of carbamazepine is rapid (30-60 minutes), and the drug is accumulated in the fetal tissues, with higher levels found in liver and kidney than in brain and lung.

Carbamazepine has been shown to have adverse effects in reproduction studies in rats when given orally in dosages 10-25 times the maximum human daily dosage (MHDD) of 1200 mg on a mg/kg basis or 1.5-4 times the MHDD on a mg/m^2 basis. In rat teratology studies, 2 of 135 offspring showed kinked ribs at 250 mg/kg and 4 of 119 offspring at 650 mg/kg showed other anomalies (cleft palate, 1; talipes, 1; anophthalmos, 2). In reproduction studies in rats, nursing offspring demonstrated a lack of weight gain and an unkempt appearance at a maternal dosage level of 200 mg/kg.

Antiepileptic drugs should not be discontinued abruptly in patients in whom the drug is administered to prevent major seizures because of the strong possibility of precipitating status epilepticus with attendant hypoxia and threat to life. In individual cases where the severity and frequency of the seizure disorder are such that removal of medication does not pose a serious threat to the patient, discontinuation of the drug may be considered prior to and during pregnancy, although it cannot be said with any confidence that even minor seizures do not pose some hazard to the developing embryo or fetus.

Tests to detect defects using currently accepted procedures should be considered a part of routine prenatal care in childbearing women receiving carbamazepine.

There have been a few cases of neonatal seizures and/or respiratory depression associated with maternal carbamazepine and other concomitant anticonvulsant drug use. A few cases of neonatal vomiting, diarrhea, and/or decreased feeding have also been reported in association with maternal carbamazepine use. These symptoms may represent a neonatal withdrawal syndrome.

To provide information regarding the effects of in utero exposure to carbamazepine, physicians are advised to recommend that pregnant patients taking carbamazepine enroll in the North American Antiepileptic Drug (NAAED) Pregnancy Registry. This can be done by calling the toll free number 1-888-233-2334, and must be done by patients themselves. Information on the registry can also be found at the website http://www.aedpregnancyregistry.org/.

PRECAUTIONS

General

Before initiating therapy, a detailed history and physical examination should be made.

Carbamazepine should be used with caution in patients with a mixed seizure disorder that includes atypical absence seizures, since in these patients carbamazepine has been associated with increased frequency of generalized convulsions (see INDICATIONS AND USAGE).

Therapy should be prescribed only after critical benefit-to-risk appraisal in patients with a history of cardiac conduction disturbance, including second and third degree AV heart block; cardiac, hepatic, or renal damage; adverse hematologic or hypersensitivity reaction to other drugs, including reactions to other anticonvulsants; or interrupted courses of therapy with carbamazepine.

AV heart block, including second and third degree block, have been reported following carbamazepine treatment. This occurred generally, but not solely, in patients with underlying EKG abnormalities or risk factors for conduction disturbances.

Hepatic effects, ranging from slight elevations in liver enzymes to rare cases of hepatic failure have been reported (see ADVERSE REACTIONS and PRECAUTIONS, Laboratory Tests). In some cases, hepatic effects may progress despite discontinuation of the drug.

Multiorgan hypersensitivity reactions which can affect the skin, liver, hemopoietic organs and lymphatic system or other organs and occurring days to weeks or months after initiating treatment have been reported in rare cases (see ADVERSE REACTIONS, Other and PRECAUTIONS, Information for Patients).

Discontinuation of carbamazepine should be considered if any evidence of hypersensitivity develops.

Hypersensitivity reactions to carbamazepine have been reported in patients who previously experienced this reaction to anticonvulsants including phenytoin and phenobarbital. A history of hypersensitivity reactions should be obtained for a patient and the immediate family members. If positive, caution should be used in prescribing carbamazepine.

In patients who have exhibited hypersensitivity reactions to carbamazepine approximately 25 to 30% of these patients may experience hypersensitivity reactions with oxcarbazepine (Trileptal®).

Since a given dose of carbamazepine suspension will produce higher peak levels than the same dose given as the tablet, it is recommended that patients given the suspension be started on lower doses and increased slowly to avoid unwanted side effects (see DOSAGE AND ADMINISTRATION).

Carbamazepine suspension contains sorbitol and, therefore, should not be administered to patients with rare hereditary problems of fructose intolerance.

Information for Patients

Patients should be made aware of the early toxic signs and symptoms of a potential hematologic problem, as well as dermatologic, hypersensitivity or hepatic reactions. These symptoms may include, but are not limited to, fever, sore throat, rash, ulcers in the mouth, easy bruising, lymphadenopathy and petechial or purpuric hemorrhage, and in the case of liver reactions, anorexia, nausea/vomiting, or jaundice. The patient should be advised that, because these signs and symptoms may signal a serious reaction, that they must report any occurrence immediately to a physician. In addition, the patient should be advised that these signs and symptoms should be reported even if mild or when occurring after extended use.

Patients, their caregivers, and families should be counseled that AEDs, including carbamazepine, may increase the risk of suicidal thoughts and behavior and should be advised of the need to be alert for the emergence or worsening of symptoms of depression, any unusual changes in mood or behavior, or the emergence of suicidal thoughts, behavior, or thoughts about self-harm. Behaviors of concern should be reported immediately to healthcare providers

Patients should be advised that serious skin reactions have been reported in association with carbamazepine. In the event a skin reaction should occur while taking carbamazepine, patients should consult with their physician immediately (see WARNINGS).

Carbamazepine may interact with some drugs. Therefore, patients should be advised to report to their doctors the use of any other prescription or nonprescription medications or herbal products.

Caution should be exercised if alcohol is taken in combination with carbamazepine therapy, due to a possible additive sedative effect.

Since dizziness and drowsiness may occur, patients should be cautioned about the hazards of operating machinery or automobiles or engaging in other potentially dangerous tasks.

Patients should be encouraged to enroll in the NAAED Pregnancy Registry if they become pregnant. This registry is collecting information about the safety of antiepileptic drugs during pregnancy. To enroll, patients can call the toll free number 1-888-233-2334 (see WARNINGS, Usage in Pregnancy subsection).

Laboratory Tests

For genetically at-risk patients (see WARNINGS), high-resolution ‘HLA-B*1502 typing’ is recommended. The test is positive if either one or two HLA-B*1502 alleles are detected and negative if no HLA-B*1502 alleles are detected.

Complete pretreatment blood counts, including platelets and possibly reticulocytes and serum iron, should be obtained as a baseline. If a patient in the course of treatment exhibits low or decreased white blood cell or platelet counts, the patient should be monitored closely. Discontinuation of the drug should be considered if any evidence of significant bone marrow depression develops.

Baseline and periodic evaluations of liver function, particularly in patients with a history of liver disease, must be performed during treatment with this drug since liver damage may occur (see PRECAUTIONS, General and ADVERSE REACTIONS). Carbamazepine should be discontinued, based on clinical judgment, if indicated by newly occurring or worsening clinical or laboratory evidence of liver dysfunction or hepatic damage, or in the case of active liver disease.

Baseline and periodic eye examinations, including slit-lamp, funduscopy, and tonometry, are recommended since many phenothiazines and related drugs have been shown to cause eye changes.

Baseline and periodic complete urinalysis and BUN determinations are recommended for patients treated with this agent because of observed renal dysfunction.

Monitoring of blood levels (see CLINICAL PHARMACOLOGY) has increased the efficacy and safety of anticonvulsants. This monitoring may be particularly useful in cases of dramatic increase in seizure frequency and for verification of compliance. In addition, measurement of drug serum levels may aid in determining the cause of toxicity when more than one medication is being used.

Thyroid function tests have been reported to show decreased values with carbamazepine administered alone.

Hyponatremia has been reported in association with carbamazepine use, either alone or in combination with other drugs.

Interference with some pregnancy tests has been reported.

Drug Interactions

There has been a report of a patient who passed an orange rubbery precipitate in his stool the day after ingesting carbamazepine suspension immediately followed by Thorazine®* solution. Subsequent testing has shown that mixing carbamazepine suspension and chlorpromazine solution (both generic and brand name) as well as carbamazepine suspension and liquid Mellaril® resulted in the occurrence of this precipitate. Because the extent to which this occurs with other liquid medications is not known, carbamazepine suspension should not be administered simultaneously with other liquid medicinal agents or diluents (see DOSAGE AND ADMINISTRATION).

Clinically meaningful drug interactions have occurred with concomitant medications and include, but are not limited to, the following:

Agents That May Affect Carbamazepine Plasma Levels

CYP 3A4 inhibitors inhibit carbamazepine metabolism and can thus increase plasma carbamazepine levels. Drugs that have been shown, or would be expected, to increase plasma carbamazepine levels include:

cimetidine, danazol, diltiazem, macrolides, erythromycin, troleandomycin, clarithromycin, fluoxetine, fluvoxamine, nefazodone, trazodone, loxapine*, olanzapine, quetiapine*, loratadine, terfenadine, omeprazole, oxybutynin, dantrolene, isoniazid, niacinamide, nicotinamide, ibuprofen, propoxyphene, azoles (e.g., ketaconazole, itraconazole, fluconazole, voriconazole), acetazolamide, verapamil, ticlopidine, grapefruit juice, protease inhibitors, valproate*.

CYP 3A4 inducers can increase the rate of carbamazepine metabolism. Drugs that have been shown, or that would be expected, to decrease plasma carbamazepine levels include:

cisplatin, doxorubicin HCl, felbamate†, fosphenytoin, rifampin, phenobarbital, phenytoin, primidone, methsuximide, theophylline, aminophylline.

When carbamazepine is given with drugs that can increase or decrease carbamazepine levels, close monitoring of carbamazepine levels is indicated and dosage adjustment may be required.

*increased levels of the active 10,11-epoxide

†decreased levels of carbamazepine and increased levels of the 10,11-epoxide

Effect of Carbamazepine on Plasma Levels of Concomitant Agents

Increased levels: clomipramine HCl, phenytoin, primidone

Carbamazepine is a potent inducer of hepatic CYP 3A4 and may therefore reduce plasma concentrations of comedications mainly metabolized by 3A4 through induction of their metabolism. Carbamazepine causes, or would be expected to cause, decreased levels of the following:

acetaminophen, alprazolam, bupropion, dihydropyridine calcium channel blockers (e.g., felodipine), citalopram, cyclosporine, corticosteroids (e.g., prednisolone, dexamethasone), clonazepam, clozapine, dicumarol, doxycycline, ethosuximide, everolimus, haloperidol, imatinib, itraconazole, lamotrigine, levothyroxine, methadone, methsuximide, midazolam, olanzapine, oral and other hormonal contraceptives, oxcarbazepine, phensuximide, phenytoin, praziquantel, protease inhibitors, risperidone, theophylline, tiagabine, topiramate, tramadol, trazodone, tricyclic antidepressants (e.g., imipramine, amitriptyline, nortriptyline), valproate, warfarin, ziprasidone, zonisamide.

In concomitant use with carbamazepine, dosage adjustment of the above agents may be necessary.

Coadministration of carbamazepine with nefazodone results in insufficient plasma concentrations of nefazodone and its active metabolite to achieve a therapeutic effect. Coadministration of carbamazepine with nefazodone is contraindicated (see CONTRAINDICATIONS).

Concomitant administration of carbamazepine and lithium may increase the risk of neurotoxic side effects.

Concomitant use of carbamazepine and isoniazid has been reported to increase isoniazid-induced hepatotoxicity.

Concomitant medication with carbamazepine and some diuretics (hydrochlorothiazide, furosemide) may lead to symptomatic hyponatremia.

Carbamazepine may antagonize the effects of nondepolarizing muscle relaxants (e.g., pancuronium).

Their dosage may need to be raised, and patients should be monitored closely for more rapid recovery from neuromuscular blockade than expected.

Alterations of thyroid function have been reported in combination therapy with other anticonvulsant medications.

Concomitant use of carbamazepine with hormonal contraceptive products (e.g., oral, and levonorgestrel subdermal implant contraceptives) may render the contraceptives less effective because the plasma concentrations of the hormones may be decreased. Breakthrough bleeding and unintended pregnancies have been reported. Alternative or back-up methods of contraception should be considered.

Carcinogenesis, Mutagenesis, Impairment of Fertility

Carbamazepine, when administered to Sprague-Dawley rats for two years in the diet at doses of 25, 75, and 250 mg/kg/day, resulted in a dose-related increase in the incidence of hepatocellular tumors in females and of benign interstitial cell adenomas in the testes of males.

Carbamazepine must, therefore, be considered to be carcinogenic in Sprague-Dawley rats. Bacterial and mammalian mutagenicity studies using carbamazepine produced negative results. The significance of these findings relative to the use of carbamazepine in humans is, at present, unknown.

Usage in Pregnancy

Pregnancy Category D (see WARNINGS).

Labor and Delivery

The effect of carbamazepine on human labor and delivery is unknown.

Nursing Mothers

Carbamazepine and its epoxide metabolite are transferred to breast milk. The ratio of the concentration in breast milk to that in maternal plasma is about 0.4 for carbamazepine and about 0.5 for the epoxide. The estimated doses given to the newborn during breast-feeding are in the range of 2-5 mg daily for carbamazepine and 1-2 mg daily for the epoxide.

Because of the potential for serious adverse reactions in nursing infants from carbamazepine, a decision should be made whether to discontinue nursing or to discontinue the drug, taking into account the importance of the drug to the mother.

Pediatric Use

Substantial evidence of carbamazepine’s effectiveness for use in the management of children with epilepsy (see INDICATIONS AND USAGE for specific seizure types) is derived from clinical investigations performed in adults and from studies in several in vitro systems which support the conclusion that (1) the pathogenetic mechanisms underlying seizure propagation are essentially identical in adults and children, and (2) the mechanism of action of carbamazepine in treating seizures is essentially identical in adults and children.

Taken as a whole, this information supports a conclusion that the generally accepted therapeutic range of total carbamazepine in plasma (i.e., 4-12 mcg/mL) is the same in children and adults.

The evidence assembled was primarily obtained from short-term use of carbamazepine. The safety of carbamazepine in children has been systematically studied up to 6 months. No longer-term data from clinical trials is available.

Geriatric Use

No systematic studies in geriatric patients have been conducted.

ADVERSE REACTIONS

If adverse reactions are of such severity that the drug must be discontinued, the physician must be aware that abrupt discontinuation of any anticonvulsant drug in a responsive epileptic patient may lead to seizures or even status epilepticus with its life-threatening hazards.

The most severe adverse reactions have been observed in the hemopoietic system and skin (see BOXED WARNING), the liver, and the cardiovascular system.

The most frequently observed adverse reactions, particularly during the initial phases of therapy, are dizziness, drowsiness, unsteadiness, nausea, and vomiting. To minimize the possibility of such reactions, therapy should be initiated at the low dosage recommended.

The following additional adverse reactions have been reported:

Hemopoietic System: Aplastic anemia, agranulocytosis, pancytopenia, bone marrow depression, thrombocytopenia, leukopenia, leukocytosis, eosinophilia, anemia, acute intermittent porphyria, variegate porphyria, porphyria cutanea tarda.

Skin: Toxic epidermal necrolysis (TEN) and Stevens-Johnson syndrome (SJS) (see BOXED WARNING), pruritic and erythematous rashes, urticaria, photosensitivity reactions, alterations in skin pigmentation, exfoliative dermatitis, erythema multiforme and nodosum, purpura, aggravation of disseminated lupus erythematosus, alopecia, and diaphoresis. In certain cases, discontinuation of therapy may be necessary. Isolated cases of hirsutism have been reported, but a causal relationship is not clear.

Cardiovascular System: Congestive heart failure, edema, aggravation of hypertension, hypotension, syncope and collapse, aggravation of coronary artery disease, arrhythmias and AV block, thrombophlebitis, thromboembolism (e.g., pulmonary embolism), and adenopathy or lymphadenopathy.

Some of these cardiovascular complications have resulted in fatalities. Myocardial infarction has been associated with other tricyclic compounds.

Liver: Abnormalities in liver function tests, cholestatic and hepatocellular jaundice, hepatitis; very rare cases of hepatic failure.

Pancreatic: Pancreatitis.

Respiratory System: Pulmonary hypersensitivity characterized by fever, dyspnea, pneumonitis, or pneumonia.

Genitourinary System: Urinary frequency, acute urinary retention, oliguria with elevated blood pressure, azotemia, renal failure, and impotence. Albuminuria, glycosuria, elevated BUN, and microscopic deposits in the urine have also been reported. There have been very rare reports of impaired male fertility and/or abnormal spermatogenesis.

Testicular atrophy occurred in rats receiving carbamazepine orally from 4-52 weeks at dosage levels of 50-400 mg/kg/day. Additionally, rats receiving carbamazepine in the diet for 2 years at dosage levels of 25, 75, and 250 mg/kg/day had a dose-related incidence of testicular atrophy and aspermatogenesis. In dogs, it produced a brownish discoloration, presumably a metabolite, in the urinary bladder at dosage levels of 50 mg/kg and higher. Relevance of these findings to humans is unknown.

Nervous System: Dizziness, drowsiness, disturbances of coordination, confusion, headache, fatigue, blurred vision, visual hallucinations, transient diplopia, oculomotor disturbances, nystagmus, speech disturbances, abnormal involuntary movements, peripheral neuritis and paresthesias, depression with agitation, talkativeness, tinnitus, hyperacusis, neuroleptic malignant syndrome.

There have been reports of associated paralysis and other symptoms of cerebral arterial insufficiency, but the exact relationship of these reactions to the drug has not been established.

Isolated cases of neuroleptic malignant syndrome have been reported both with and without concomitant use of psychotropic drugs.

Digestive System: Nausea, vomiting, gastric distress and abdominal pain, diarrhea, constipation, anorexia, and dryness of the mouth and pharynx, including glossitis and stomatitis.

Eyes: Scattered punctate cortical lens opacities, increased intraocular pressure as well as conjunctivitis, have been reported. Although a direct causal relationship has not been established, many phenothiazines and related drugs have been shown to cause eye changes.

Musculoskeletal System: Aching joints and muscles, and leg cramps.

Metabolism: Fever and chills. Inappropriate antidiuretic hormone (ADH) secretion syndrome has been reported. Cases of frank water intoxication, with decreased serum sodium (hyponatremia) and confusion, have been reported in association with carbamazepine use (see PRECAUTIONS, Laboratory Tests). Decreased levels of plasma calcium leading to osteoporosis have been reported.

Other: Multiorgan hypersensitivity reactions occurring days to weeks or months after initiating treatment have been reported in rare cases. Signs or symptoms may include, but are not limited to fever, skin rashes, vasculitis, lymphadenopathy, disorders mimicking lymphoma, arthralgia, leukopenia, eosinophilia, hepatosplenomegaly and abnormal liver function tests. These signs and symptoms may occur in various combinations and not necessarily concurrently. Signs and symptoms may initially be mild. Various organs, including but not limited to, liver, skin, immune system, lungs, kidneys, pancreas, myocardium, and colon may be affected (see PRECAUTIONS, General and PRECAUTIONS, Information for Patients).

Isolated cases of a lupus erythematosus-like syndrome have been reported. There have been occasional reports of elevated levels of cholesterol, HDL cholesterol, and triglycerides in patients taking anticonvulsants.

A case of aseptic meningitis, accompanied by myoclonus and peripheral eosinophilia, has been reported in a patient taking carbamazepine in combination with other medications. The patient was successfully dechallenged, and the meningitis reappeared upon rechallenge with carbamazepine.

DRUG ABUSE AND DEPENDENCE

No evidence of abuse potential has been associated with carbamazepine, nor is there evidence of psychological or physical dependence in humans.

OVERDOSAGE

Acute Toxicity

Lowest known lethal dose: adults, 3.2 g (a 24-year-old woman died of a cardiac arrest and a 24-year-old man died of pneumonia and hypoxic encephalopathy); children, 4 g (a 14-year-old girl died of a cardiac arrest), 1.6 g (a 3-year-old girl died of aspiration pneumonia).

Oral LD50 in animals (mg/kg): mice, 1100-3750; rats, 3850-4025; rabbits, 1500-2680; guinea pigs, 920.

Signs and Symptoms

The first signs and symptoms appear after 1-3 hours. Neuromuscular disturbances are the most prominent. Cardiovascular disorders are generally milder, and severe cardiac complications occur only when very high doses (>60 g) have been ingested.

Respiration: Irregular breathing, respiratory depression.

Cardiovascular System: Tachycardia, hypotension or hypertension, shock, conduction disorders.

Nervous System and Muscles: Impairment of consciousness ranging in severity to deep coma. Convulsions, especially in small children. Motor restlessness, muscular twitching, tremor, athetoid movements, opisthotonos, ataxia, drowsiness, dizziness, mydriasis, nystagmus, adiadochokinesia, ballism, psychomotor disturbances, dysmetria. Initial hyperreflexia, followed by hyporeflexia.

Gastrointestinal Tract: Nausea, vomiting.

Kidneys and Bladder: Anuria or oliguria, urinary retention.

Laboratory Findings: Isolated instances of overdosage have included leukocytosis, reduced leukocyte count, glycosuria, and acetonuria. EEG may show dysrhythmias.

Combined Poisoning: When alcohol, tricyclic antidepressants, barbiturates, or hydantoins are taken at the same time, the signs and symptoms of acute poisoning with carbamazepine may be aggravated or modified.

Treatment

The prognosis in cases of severe poisoning is critically dependent upon prompt elimination of the drug, which may be achieved by inducing vomiting, irrigating the stomach, and by taking appropriate steps to diminish absorption. If these measures cannot be implemented without risk on the spot, the patient should be transferred at once to a hospital, while ensuring that vital functions are safeguarded. There is no specific antidote.

Elimination of the Drug: Induction of vomiting.

Gastric lavage. Even when more than 4 hours have elapsed following ingestion of the drug, the stomach should be repeatedly irrigated, especially if the patient has also consumed alcohol.

Measures to Reduce Absorption: Activated charcoal, laxatives.

Measures to Accelerate Elimination: Forced diuresis.

Dialysis is indicated only in severe poisoning associated with renal failure. Replacement transfusion is indicated in severe poisoning in small children.

Respiratory Depression: Keep the airways free; resort, if necessary, to endotracheal intubation, artificial respiration, and administration of oxygen.

Hypotension, Shock: Keep the patient’s legs raised and administer a plasma expander. If blood pressure fails to rise despite measures taken to increase plasma volume, use of vasoactive substances should be considered.

Convulsions: Diazepam or barbiturates.

Warning: Diazepam or barbiturates may aggravate respiratory depression (especially in children), hypotension, and coma. However, barbiturates should not be used if drugs that inhibit monoamine oxidase have also been taken by the patient either in overdosage or in recent therapy (within 1 week).

Surveillance: Respiration, cardiac function (ECG monitoring), blood pressure, body temperature, pupillary reflexes, and kidney and bladder function should be monitored for several days.

Treatment of Blood Count Abnormalities: If evidence of significant bone marrow depression develops, the following recommendations are suggested: (1) stop the drug, (2) perform daily CBC, platelet, and reticulocyte counts, (3) do a bone marrow aspiration and trephine biopsy immediately and repeat with sufficient frequency to monitor recovery.

Special periodic studies might be helpful as follows: (1) white cell and platelet antibodies, (2) ^59Fe-ferrokinetic studies, (3) peripheral blood cell typing, (4) cytogenetic studies on marrow and peripheral blood, (5) bone marrow culture studies for colony-forming units, (6) hemoglobin electrophoresis for A2 and F hemoglobin, and (7) serum folic acid and B12 levels.

A fully developed aplastic anemia will require appropriate, intensive monitoring and therapy, for which specialized consultation should be sought.

DOSAGE AND ADMINISTRATION

Carbamazepine suspension in combination with liquid chlorpromazine or thioridazine results in precipitate formation, and, in the case of chlorpromazine, there has been a report of a patient passing an orange rubbery precipitate in the stool following coadministration of the two drugs (see PRECAUTIONS, Drug Interactions). Because the extent to which this occurs with other liquid medications is not known, carbamazepine suspension should not be administered simultaneously with other liquid medications or diluents.

Monitoring of blood levels has increased the efficacy and safety of anticonvulsants (see PRECAUTIONS, Laboratory Tests). Dosage should be adjusted to the needs of the individual patient. A low initial daily dosage with a gradual increase is advised. As soon as adequate control is achieved, the dosage may be reduced very gradually to the minimum effective level. Medication should be taken with meals.

Since a given dose of carbamazepine suspension will produce higher peak levels than the same dose given as the tablet, it is recommended to start with low doses (children 6-12 years: 1/2 teaspoon q.i.d.) and to increase slowly to avoid unwanted side effects.

Conversion of patients from oral carbamazepine tablets to carbamazepine suspension: Patients should be converted by administering the same number of mg per day in smaller, more frequent doses (i.e., b.i.d. tablets to t.i.d. suspension).

Carbamazepine extended-release is an extended-release formulation for twice-a-day administration. When converting patients from carbamazepine conventional tablets to carbamazepine extended-release, the same total daily mg dose of carbamazepine extended-release should be administered. Carbamazepine extended-release tablets must be swallowed whole and never crushed or chewed. Carbamazepine extended-release tablets should be inspected for chips or cracks. Damaged tablets, or tablets without a release portal, should not be consumed. Carbamazepine extended-release tablet coating is not absorbed and is excreted in the feces; these coatings may be noticeable in the stool.

Epilepsy (SEE INDICATIONS AND USAGE)

Adults and children over 12 years of age - Initial: Either 200 mg b.i.d. for tablets and extended-release tablets, or 1 teaspoon q.i.d. for suspension (400 mg/day). Increase at weekly intervals by adding up to 200 mg/day using a b.i.d. regimen of carbamazepine extended-release or a t.i.d. or q.i.d. regimen of the other formulations until the optimal response is obtained. Dosage generally should not exceed 1000 mg daily in children 12-15 years of age, and 1200 mg daily in patients above 15 years of age. Doses up to 1600 mg daily have been used in adults in rare instances. Maintenance: Adjust dosage to the minimum effective level, usually 800-1200 mg daily.

Children 6-12 years of age - Initial: Either 100 mg b.i.d. for tablets or extended-release tablets, or 1/2 teaspoon q.i.d. for suspension (200 mg/day). Increase at weekly intervals by adding up to 100 mg/day using a b.i.d. regimen of carbamazepine extended-release or a t.i.d. or q.i.d. regimen of the other formulations until the optimal response is obtained. Dosage generally should not exceed 1000 mg daily. Maintenance: Adjust dosage to the minimum effective level, usually 400-800 mg daily.

Children under 6 years of age - Initial: 10-20 mg/kg/day b.i.d. or t.i.d. as tablets, or q.i.d. as suspension. Increase weekly to achieve optimal clinical response administered t.i.d. or q.i.d. Maintenance: Ordinarily, optimal clinical response is achieved at daily doses below 35 mg/kg. If satisfactory clinical response has not been achieved, plasma levels should be measured to determine whether or not they are in the therapeutic range. No recommendation regarding the safety of carbamazepine for use at doses above 35 mg/kg/24 hours can be made.

Combination Therapy: Carbamazepine may be used alone or with other anticonvulsants. When added to existing anticonvulsant therapy, the drug should be added gradually while the other anticonvulsants are maintained or gradually decreased, except phenytoin, which may have to be increased (see PRECAUTIONS, Drug Interactions, and Pregnancy Category D).

Trigeminal Neuralgia (SEE INDICATIONS AND USAGE)

Initial: On the first day, either 100 mg b.i.d. for tablets or extended-release tablets, or 1/2 teaspoon q.i.d. for suspension, for a total daily dose of 200 mg. This daily dose may be increased by up to 200 mg/day using increments of 100 mg every 12 hours for tablets or extended-release tablets, or 50 mg (1/2 teaspoon) q.i.d. for suspension, only as needed to achieve freedom from pain. Do not exceed 1200 mg daily. Maintenance: Control of pain can be maintained in most patients with 400-800 mg daily. However, some patients may be maintained on as little as 200 mg daily, while others may require as much as 1200 mg daily. At least once every 3 months throughout the treatment period, attempts should be made to reduce the dose to the minimum effective level or even to discontinue the drug.

Dosage Information
 | Initial Dose | Subsequent Dose | Maximum Daily Dose
Indication | Tablet* | extended-release tablets | Suspension | Tablet* | extended-release tablets | Suspension | Tablet* | extended-release tablets | Suspension
Epilepsy Under 6 yr | 10-20 mg/kg/day b.i.d. or t.i.d. |  | 10-20 mg/kg/day q.i.d. | Increase weekly to achieve optimal clinical response, t.i.d. or q.i.d. |  | Increase weekly to achieve optimal clinical response, t.i.d. or q.i.d. | 35 mg/kg/24 hr (see Dosage and Administration section above) |  | 35 mg/kg/24 hr (see Dosage and Administration section above)
6-12 yr | 100 mg b.i.d. (200 mg/day) | 100 mg b.i.d. (200 mg/day) | ½ tsp q.i.d. (200 mg/day) | Add up to 100 mg/day at weekly intervals, t.i.d. or q.i.d. | Add 100 mg/day at weekly intervals, b.i.d. | Add up to 1 tsp (100 mg)/day at weekly intervals, t.i.d. or q.i.d. |  | 1000 mg/24 hr
Over 12 yr | 200 mg b.i.d. (400 mg/day) | 200 mg b.i.d. (400 mg/day) | 1 tsp q.i.d. (400 mg/day) | Add up to 200 mg/day at weekly intervals, t.i.d. or q.i.d. | Add up to 200 mg/day at weekly intervals, b.i.d. | Add up to 2 tsp (200 mg)/day at weekly intervals, t.i.d. or q.i.d. | 1000 mg/24 hr (12-15 yr) 1200 mg/24 hr (>15 yr) 1600 mg/24 hr (adults, in rare instances)
Trigeminal Neuralgia | 100 mg b.i.d. (200 mg/day) | 100 mg b.i.d. (200 mg/day) | ½ tsp q.i.d. (200 mg/day) | Add up to 200 mg/day in increments of 100 mg every 12 hr | Add up to 200 mg/day in increments of 100 mg every 12 hr | Add up to 2 tsp (200 mg)/day in increments of 50 mg (½ tsp) q.i.d. |  | 1200 mg/24 hr

*Tablet = Chewable or conventional tablets

HOW SUPPLIED

Carbamazepine extended-release Tablets 400 mg - round, brown, coated (imprinted T on one side and 400 mg on the other), release portal on one side

Bottles of 30 NDC 54868-6074-0

Store at 25°C (77°F); excursions permitted to 15°- 30°C (59°F-86°F).

[see USP Controlled Room Temperature]..

Protect from moisture.

Dispense in tight container (USP).

*Thorazine® is a registered trademark of GlaxoSmithKline.

JUNE 2009 Printed in U.S.A. T2009-59

5002199

Sandoz Inc.

Princeton, NJ 08540

Repackaging and Relabeling by:
Physicians Total Care, Inc.
Tulsa, OK 74146

PRINCIPAL DISPLAY PANEL

Carbamazepine Extended-Release Tablets, USP

Package Label – 400 mg

Tablets must be swallowed whole and

never crushed or chewed.

Dispense in tight container (USP).